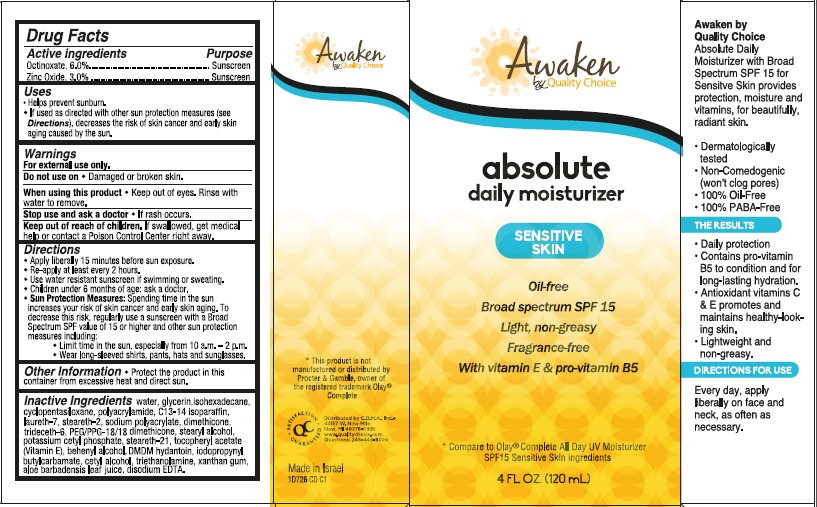 DRUG LABEL: Awaken by Quality Choice Absolute Daily Moisturizer Broad Spectrum SPF 15 Sunscreen
NDC: 63868-256 | Form: CREAM
Manufacturer: Chain Drug Marketing Association
Category: otc | Type: HUMAN OTC DRUG LABEL
Date: 20140918

ACTIVE INGREDIENTS: OCTINOXATE 6 g/100 g; ZINC OXIDE 3 g/100 g
INACTIVE INGREDIENTS: WATER; GLYCERIN; ISOHEXADECANE; CYCLOMETHICONE 5; C13-14 ISOPARAFFIN; LAURETH-7; STEARETH-2; DIMETHICONE; TRIDECETH-6; PEG/PPG-18/18 DIMETHICONE; STEARYL ALCOHOL; POTASSIUM CETYL PHOSPHATE; STEARETH-21; .ALPHA.-TOCOPHEROL ACETATE; DOCOSANOL; DMDM HYDANTOIN; IODOPROPYNYL BUTYLCARBAMATE; CETYL ALCOHOL; TROLAMINE; XANTHAN GUM; ALOE VERA LEAF; EDETATE DISODIUM

Awaken by Quality Choice absolute daily moisturizer

Active ingredient

Octinoxate, 6.0%

Zinc Oxide, 3.0%

Purpose

Sunscreen

Uses

- Helps prevent sunburn.
- If used as directed with other sun protection measures (see Directions), decreases the risk of skin cancer and early skin aging caused by the sun.

Warnings

For external use only.

Do not use on

- Damaged or broken skin.

When using this product

- Keep out of eyes. Rinse with water to remove.

Stop use and ask a doctor

- If rash occurs.

Keep Out of Reach of Children.

If swallowed, get medical help or contact a Poison Control Center right away.

Directions

- Apply liberally 15 minutes before sun exposure.
- Re-apply at least every 2 hours.
- Use water resistant sunscreen if swimming or sweating.
- Children under 6 months of age: ask a doctor.
- Sun Protection Measures: Spending time in the sun increases your risk of skin cancer and early skin aging. To decrease this risk, regularly use a sunscreen with a Broad Spectrum SPF value of 15 or higher and other sun protection measures including:
  - Limit time in the sun, especially from 10 a.m. – 2 p.m.
  - Wear long-sleeved shirts, pants, hats and sunglasses.

Other Information

- Protect the product in this container from excessive heat and direct sun.

Inactive ingredients

water, glycerin, isohexadecane, cyclopentasiloxane, polyacrylamide, C 13-14 isoparaffin, laureth-7, steareth-2, sodium polyacrylate, dimethicone, trideceth-6, PEG/PPG-18/18 dimethicone, stearyl alcohol, potassium cetyl phosphate, steareth-21, tocopheryl acetate (Vitamin E), behenyl alcohol, DMDM hydantoin, iodopropynyl butylcarbamate, cetyl alcohol, triethanolamine, xanthan gum, aloe barbadensis leaf juice, disodium EDTA.

Package/Label Principal Display Panel

Awaken
by Quality Choice

absolute
daily moisturizer

SENSITIVE SKIN

Oil-free
Broad spectrum SPF 15
Light, non-greasy
Fragrance-free
With vitamin E & pro-vitamin B5

*Compare to Olay® Complete All Day UV Moisturizer
SPF15 Sensitive Skin ingredients

4 FL OZ. (120 mL)

Awaken by Quality Choice
Absolute Daily Moisturizer with Broad Spectrum SPF 15 for Sensitive Skin provides protection, moisture and vitamins, for beautifully, radiant skin.

- Dermatologically tested
- Non-Comedogenic (won’t clog pores)
- 100% Oil-Free
- 100% PABA-Free

THE RESULTS

- Daily protection
- Contains pro-vitamin B5 to condition and for long-lasting hydration.
- Antioxidant vitamins C & E promotes and maintains healthy-looking skin.
- Lightweight and non-greasy.

DIRECTIONS FOR USE

Every day, apply liberally on face and neck as often as necessary.

*This product is not manufactured or distributed by Procter & Gamble, owner of the registered trademark Olay® Complete.

Satisfaction
Guaranteed

Distributed by C.D.M.A., Inc.©
43157 W. Nine Mile
Novi, MI 48376-0995
www.qualitychoice.com
Questions: 248-449-9300

Made in Israel
1D726 CD C1

Carton Label